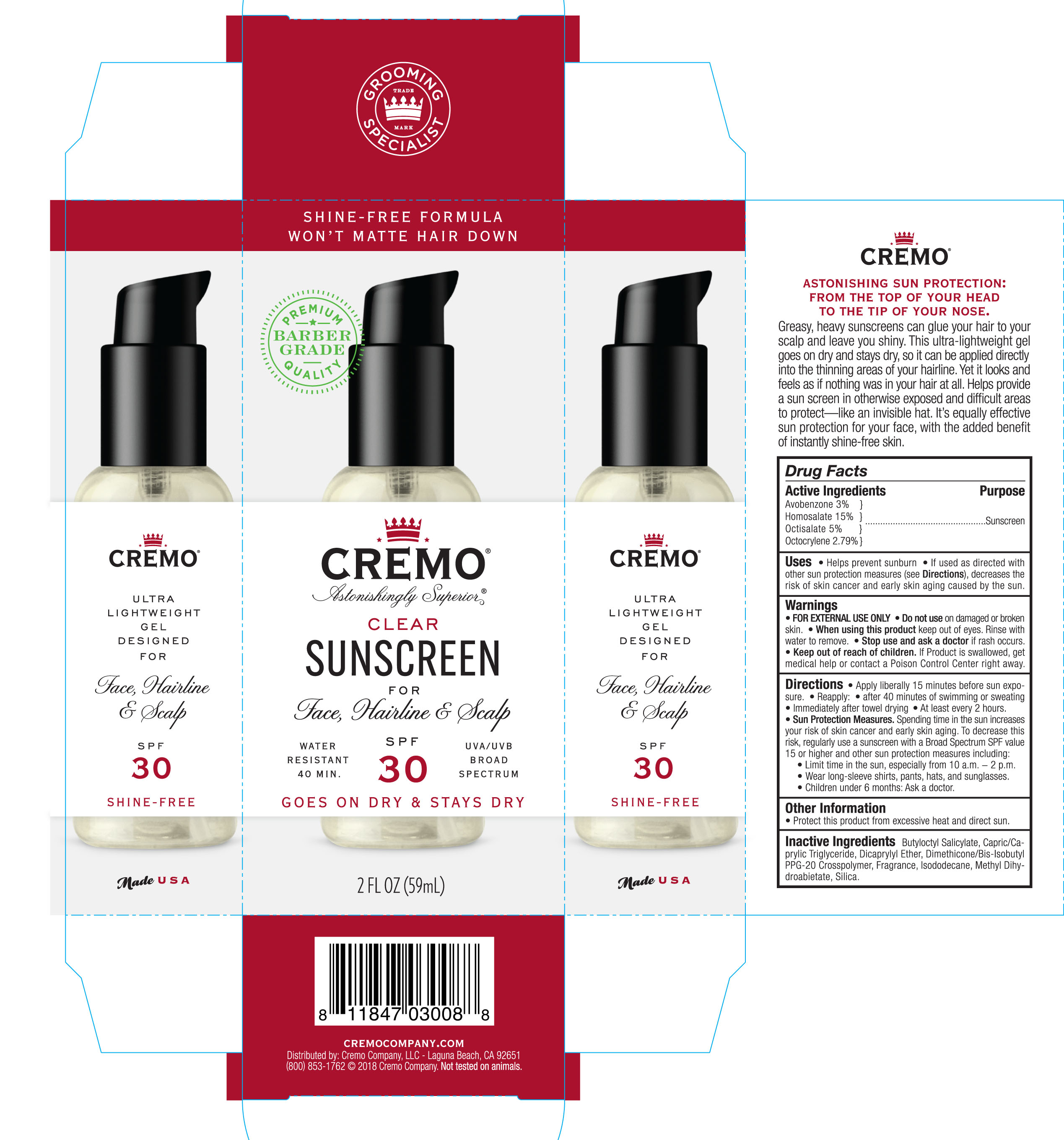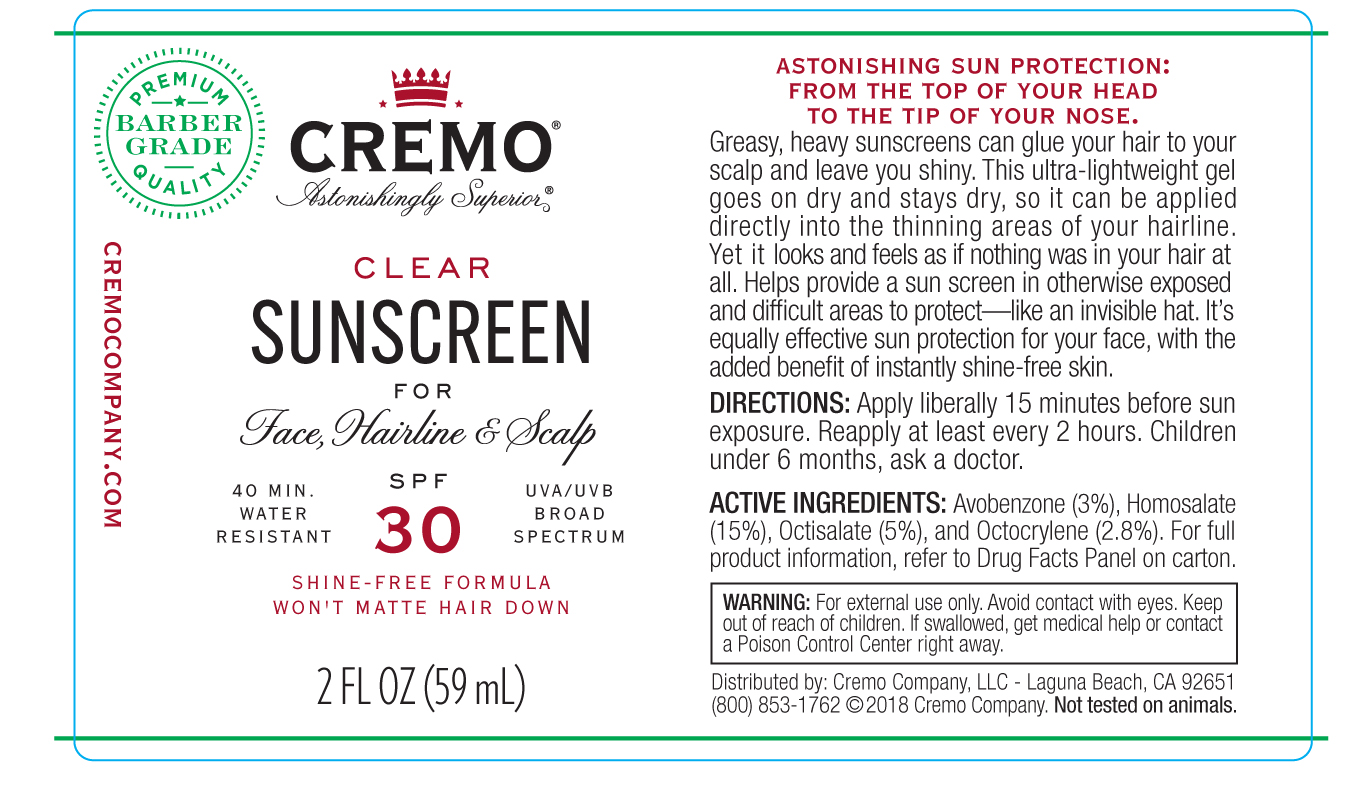 DRUG LABEL: Clear Sunscreen SPF 30 Broad Spectrum
NDC: 71825-101 | Form: GEL
Manufacturer: Cremo company
Category: otc | Type: HUMAN OTC DRUG LABEL
Date: 20190107

ACTIVE INGREDIENTS: AVOBENZONE 3 g/100 mL; HOMOSALATE 15 g/100 mL; OCTISALATE 5 g/100 mL; OCTOCRYLENE 2.79 g/100 mL
INACTIVE INGREDIENTS: ISODODECANE; SILICON DIOXIDE; BUTYLOCTYL SALICYLATE; MEDIUM-CHAIN TRIGLYCERIDES; DICAPRYLYL ETHER; DIMETHICONE/BIS-ISOBUTYL PPG-20 CROSSPOLYMER; METHYL DIHYDROABIETATE

Clear Sunscreen SPF 30 Broad Spectrum

Active ingredients Purpose

Avobenzone 3% Sunscreen

Homoslatate 15% Sunscreen

Octisalate 5% Sunscreen

Octocrylene 2.79% Sunscreen

Uses

- Helps prvent sunburn
- If used as directed with other sun protection measures (see Directions) decreases the risk of skin cancer and early skin aging caused by the sun.

- Keep out of reach of children. If product is swallowed, get medical help or contact a poison control center right away.

Stop use and ask a doctor if rash occurs.

Warnings

- For external use only
- Do not use on broken or damaged skin
- When using this product keep out of eyes. Rinse with water to remove.

Directions

- Apply liberally 15 minutes before sun exposure
- Reapply:
- After 40 minutes of swimming or sweating
- at least every 2 hours
- Sun Protections Measures. Spending time in the sun increases your risk of skin cancer and early skin aging. To decrease this risk, regularly use a sunscreen with a Broad Spectrum SPF value of 15 or higher and other sun protection measures including:
- limit time in the sun, especially from 10 am- 2pm
- wear long-sleeve shirts, pants, hats, and sunglasses
- Children under 6 months: Ask a doctor

INACTIVE INGREDIENT

Inactive ingredients Butyloctyl Salicylate, Capric/Caprylic Triglyceride, Dicaprylyl Ether, DImethicone/Bis-Isobutyl PPG-20 Crosspolymer, Fragrance, Isododecane, Methyl Dihydroabietate, Silica.

PACKAGE LABEL

Cremo Clear Sunscreen

for face, hairline & Scalp

SPF 30 Broad Spectrum

2 FL OZ (59mL)